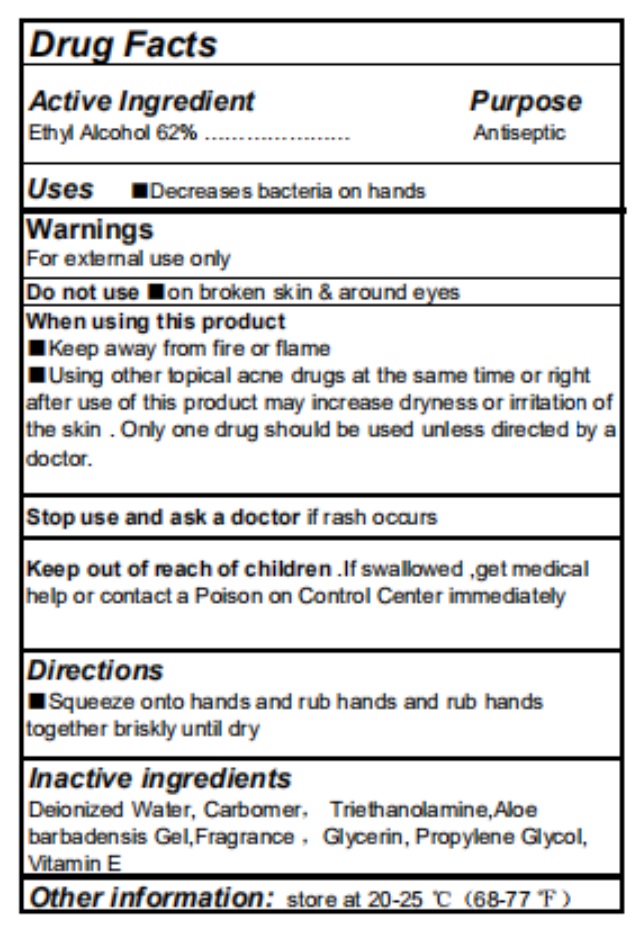 DRUG LABEL: Hand Sanitizer
NDC: 76897-001 | Form: GEL
Manufacturer: NingBo Laiao Daily Chemical Co, Ltd.
Category: otc | Type: HUMAN OTC DRUG LABEL
Date: 20200525

ACTIVE INGREDIENTS: ALCOHOL 62 mL/100 mL
INACTIVE INGREDIENTS: CARBOMER HOMOPOLYMER, UNSPECIFIED TYPE; PROPYLENE GLYCOL; WATER; GLYCERIN; .ALPHA.-TOCOPHEROL; ALOE VERA LEAF; TROLAMINE

76897-001 Hand Sanitizer 62% Alcohol

Active Ingredient

Ethyl Alcohol 62%

Purpose

Antiseptic

Use

Decreases bacteria on hands

WARNINGS

For external use only

Do not use ■on broken skin & around eyes

When using this product

■Keep away from fire or flame

■Using other topical acne drugs at the same time or right

after use of this product may increase dryness or irritation of

the skin . Only one drug should be used unless directed by a

doctor.

Stop use and ask a doctor if rash occurs

Keep out of reach of children .If swallowed ,get medical

help or contact a Poison on Control Center immediately

Directions

Squeeze onto hands and rub hands and rub hands

together briskly until dry

Inactive ingredients

Deionized Water, Carbomer， Triethanolamine,Aloe

barbadensis Gel,Fragrance ，Glycerin, Propylene Glycol,

Vitamin E